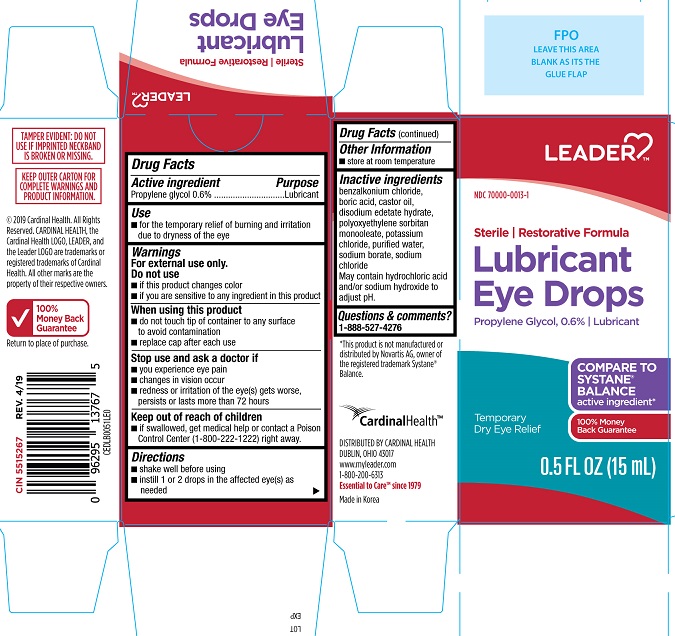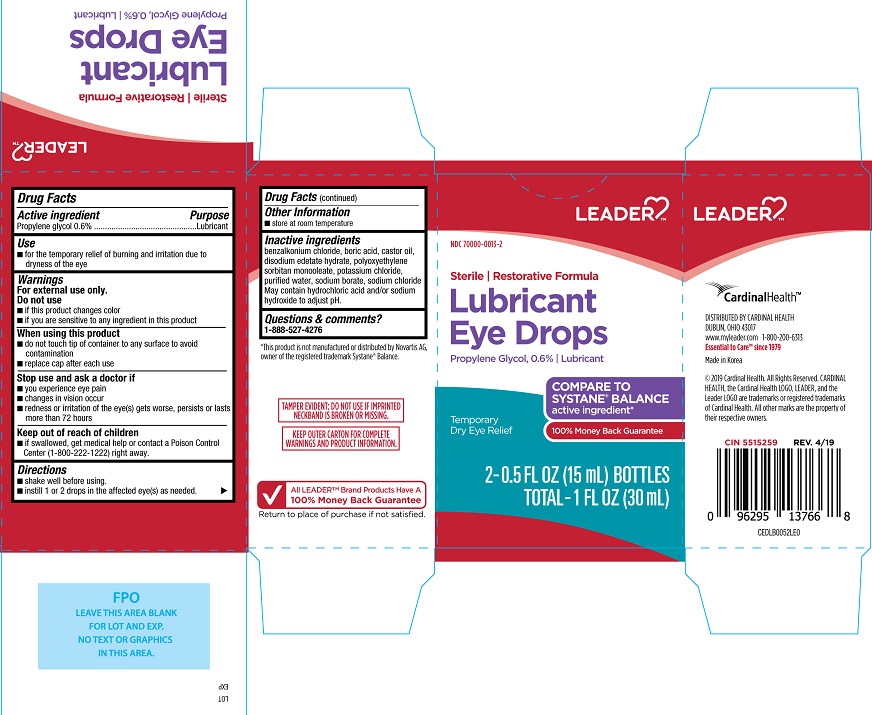 DRUG LABEL: Leader Restorative Formula Lubricant Eye Drops
NDC: 70000-0013 | Form: SOLUTION/ DROPS
Manufacturer: Cardinal Health
Category: otc | Type: HUMAN OTC DRUG LABEL
Date: 20250801

ACTIVE INGREDIENTS: PROPYLENE GLYCOL 0.6 g/100 mL
INACTIVE INGREDIENTS: BENZALKONIUM CHLORIDE; BORIC ACID; CASTOR OIL; EDETATE DISODIUM; PEG-6 SORBITAN OLEATE; POTASSIUM CHLORIDE; WATER; SODIUM BORATE; SODIUM CHLORIDE

Leader Restorative Formula Lubricant Eye Drops (PLD)

Active ingredients

Propylene glycol....0.6%

Purpose

Propylene glycol............ Lubricant

Uses
• for the temporary relief of burning and irritation due to dryness of the eye

Warnings
For external use only

Do not use
• if this product changes color
• if you are sensitive to any ingredient in this product

When using this product
• do not touch tip of container to any surface to avoid contamination
• replace cap after each use

Stop use and ask a doctor if
• you experience eye pain
• changes in vision occur
• redness or irritation of the eye(s) gets worse, persists or lasts more than 72 hours

Keep out of reach of children
If swallowed, get medical help or contact a Poison Control Center (1-800-222-1222) right away.

Directions

- Shake well before using.
- Instill 1 or 2 drops in the affected eye(s) as needed

Other information

- Store at room temperature.

Inactive ingredients

Benzalkonium chloride, boric acid, castor oil, disodium edetate hydrate, polyoxyethylene sorbitan monooleate, potassium chloride, purified water, sodium borate, sodium chloride. May contain hydrochloric acid and/or sodium hydroxide to adjust pH.

Questions & comments?

1-888-527-4276